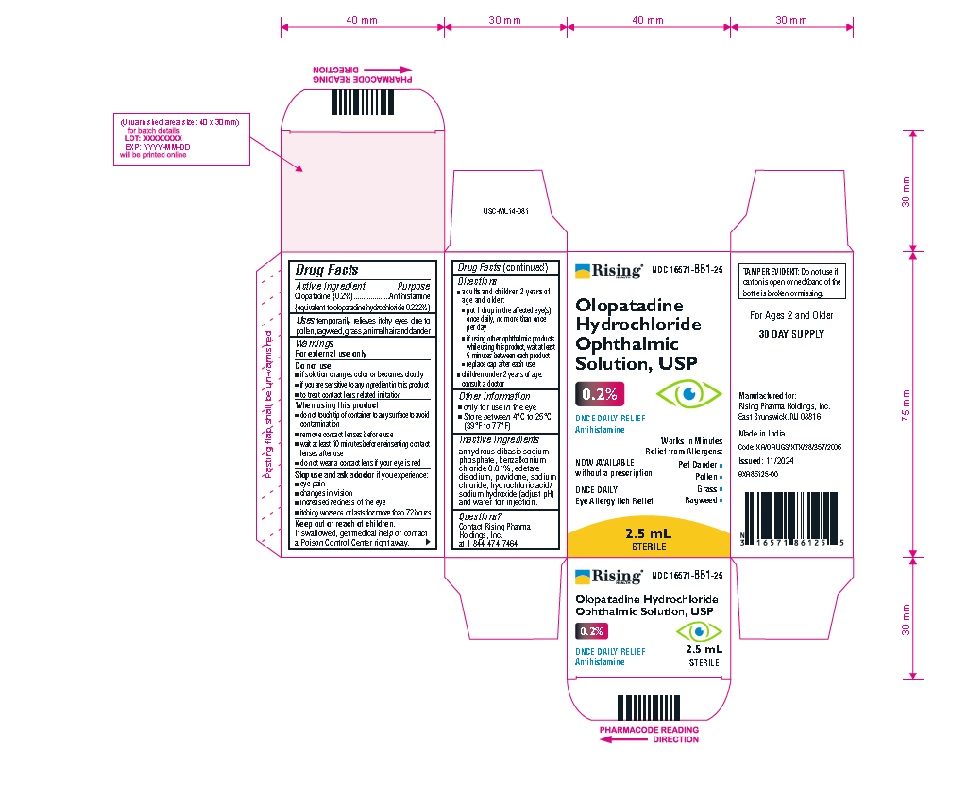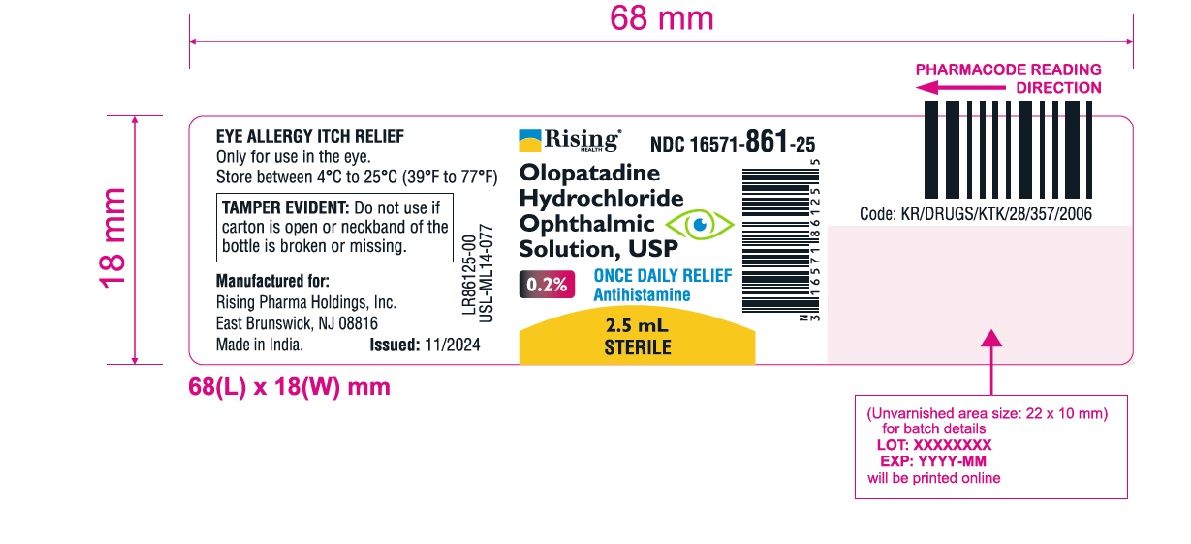 DRUG LABEL: olopatadine hydrochloride
NDC: 16571-861 | Form: SOLUTION
Manufacturer: Rising Pharma Holdings, Inc.
Category: otc | Type: Human OTC Drug Label
Date: 20250404

ACTIVE INGREDIENTS: OLOPATADINE HYDROCHLORIDE 2 mg/1 mL
INACTIVE INGREDIENTS: BENZALKONIUM CHLORIDE; EDETATE DISODIUM; SODIUM PHOSPHATE, DIBASIC, ANHYDROUS; SODIUM CHLORIDE; HYDROCHLORIC ACID; SODIUM HYDROXIDE; WATER; POVIDONE K30

Olopatadine Hydrochloride Ophthalmic Solution, USP 0.2%

ACTIVE INGREDIENT(S)

Olopatadine (0.2%) (equivalent to olopatadine hydrochloride 0.222%)

PURPOSE

Antihistamine

USE(S)

temporarily relieves itchy eyes due to pollen, ragweed, grass, animal hair and dander

WARNINGS

For external use only

DO NOT USE

▪ if solution changes color or becomes cloudy
▪ if you are sensitive to any ingredient in this product
▪ to treat contact lens related irritation

WHEN USING THIS PRODUCT

▪ do not touch tip of container to any surface to avoid contamination
▪ remove contact lenses before use
▪ wait at least 10 minutes before reinserting contact lenses after use
▪ do not wear a contact lens if your eye is red

STOP USE AND ASK DOCTOR IF

you experience:
▪ eye pain
▪ changes in vision
▪ increased redness of the eye
▪ itching worsens or lasts for more than 72 hours

KEEP OUT OF REACH OF CHILDREN

If swallowed, get medical help or contact a Poison Control Center right away.

DIRECTIONS

▪ adults and children 2 years of age and older:
▪ put 1 drop in the affected eyes(s) once daily, no more than once per day
▪ if using other ophthalmic products while using this product, wait at least 5 minutes between each product
▪ replace cap after each use
▪ children under 2 years of age: consult a doctor

Other information

▪ only for use in the eye
▪ Store between 4°C to 25°C (39°F to 77°F)

Inactive ingredients

anhydrous dibasic sodium phosphate, benzalkonium chloride 0.01%, edetate disodium, povidone, sodium chloride, hydrochloric acid/sodium hydroxide (adjust pH) and water for injection.

Questions?

Contact Rising Pharma Holdings, Inc. at 1-844-474-7464

PRINCIPAL DISPLAY PANEL

Rising NDC 16571-861-25
Olopatadine Hydrochloride Ophthalmic Solution, USP 0.2%

ONCE DAILY RELIEF Antihistamine

NOW AVAILABLE without a prescription
ONCE DAILY

Eye Allergy Itch Relief

Works in Minutes

Relief from Allergens:
•Pet Dander

•Pollen

•Grass

•Ragweed

2.5 mL STERILE

Rising NDC 16571-861-25

Olopatadine Hydrochloride Ophthalmic Solution, USP
0.2%
ONCE DAILY RELIEF Antihistamine
Eye Allergy Itch Relief
ONCE DAILY
2.5 mL
STERILE